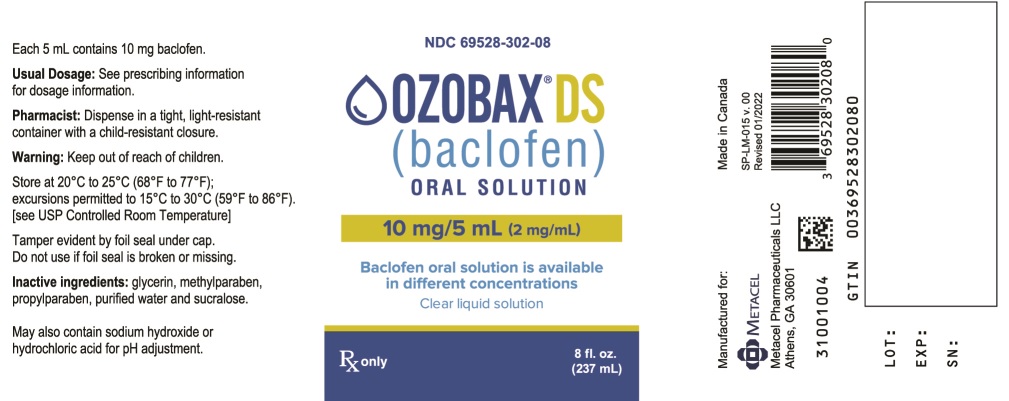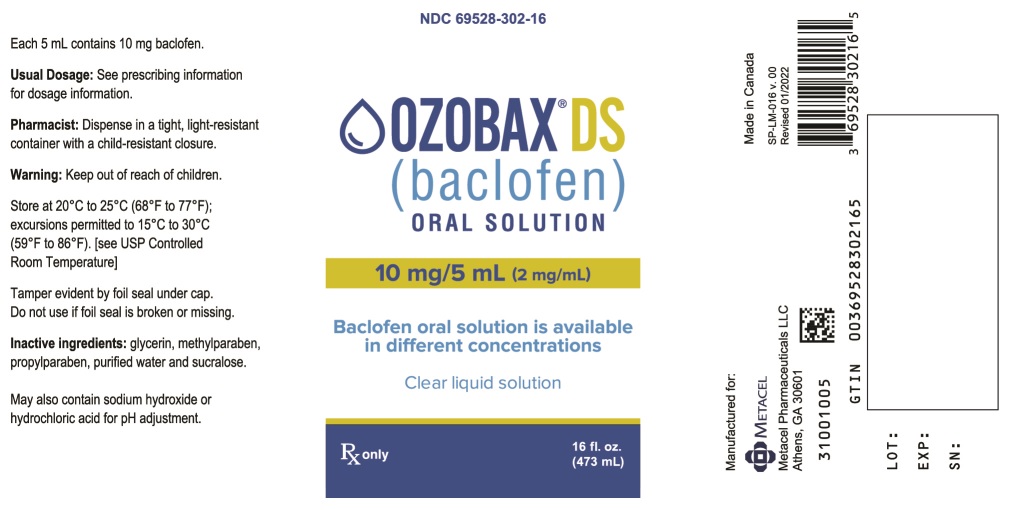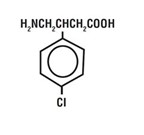 DRUG LABEL: OZOBAX
NDC: 69528-302 | Form: SOLUTION
Manufacturer: Metacel Pharmaceuticals, LLC
Category: prescription | Type: HUMAN PRESCRIPTION DRUG LABEL
Date: 20231017

ACTIVE INGREDIENTS: BACLOFEN 10 mg/5 mL
INACTIVE INGREDIENTS: GLYCERIN; METHYLPARABEN; PROPYLPARABEN; SUCRALOSE; WATER

HIGHLIGHTS OF PRESCRIBING INFORMATION

These highlights do not include all the information needed to use OZOBAX® DS safely and effectively. See full prescribing information for OZOBAX DS.
OZOBAX DS (baclofen) oral solution
Initial U.S. Approval: 1977

1 INDICATIONS AND USAGE

- OZOBAX DS is a gamma-aminobutyric acid (GABA-ergic) agonist indicated for the treatment of spasticity resulting from multiple sclerosis, particularly for the relief of flexor spasms and concomitant pain, clonus, and muscular rigidity. (1)
- OZOBAX DS may also be of some value in patients with spinal cord injuries and other spinal cord diseases. (1)

Limitations of Use

OZOBAX DS is not indicated in the treatment of skeletal muscle spasm resulting from rheumatic disorders (1)

2 DOSAGE AND ADMINISTRATION

- Baclofen oral solution is available in multiple concentrations; include both the total dose in mg and the total dose in volume on prescriptions (2.1)
- Initiate OZOBAX DS with a low dosage, preferably in divided doses, administered orally. Increase gradually based on clinical response and tolerability. (2.2)
- The maximum dosage is 80 mg daily (20 mg four times a day). (2.2)
- When discontinuing, reduce the dosage slowly. (2.3)

3 DOSAGE FORMS AND STRENGTHS

Oral Solution: 10 mg/5 mL (3)

4 CONTRAINDICATIONS

- Hypersensitivity to baclofen (4)

5 WARNINGS AND PRECAUTIONS

- Abrupt discontinuation of baclofen has resulted in serious adverse reactions including death; therefore, reduce the dosage slowly when OZOBAX DS is discontinued. (5.1)
- Neonatal withdrawal symptoms can occur; gradually reduce the dosage and discontinue OZOBAX DS before delivery. (5.2)
- OZOBAX DS can cause drowsiness and sedation. Patients should avoid the operation of automobiles or other dangerous machinery until they know how the drug affects them. Advise patients that the central nervous system effects of OZOBAX DS may be additive to those of alcohol and other CNS depressants. (5.3)
- OZOBAX DS can cause exacerbation of the following: psychotic disorders, schizophrenia, or confusional states; autonomic dysreflexia; epilepsy. Use with caution in patients with these conditions (5.5, 5.6, 5.7)

6 ADVERSE REACTIONS

- The most common (up to 15% or more) adverse reactions in patients were drowsiness, dizziness, and weakness. (6.1)

To report SUSPECTED ADVERSE REACTIONS, contact Metacel Pharmaceuticals, LLC at 1-833-469-6229 or FDA at 1-800-FDA-1088 or www.fda.gov/medwatch.

8 USE IN SPECIFIC POPULATIONS

- Pregnancy: Based on animal data, may cause fetal harm (8.1)
- Because baclofen is excreted unchanged through the kidneys it may be necessary to reduce the dosage in patients with impaired renal function. (8.6)

FULL PRESCRIBING INFORMATION

1 INDICATIONS AND USAGE

OZOBAX DS is indicated for the treatment of spasticity resulting from multiple sclerosis, particularly for the relief of flexor spasms and concomitant pain, clonus, and muscular rigidity.

OZOBAX DS may also be of some value in patients with spinal cord injuries and other spinal cord diseases.

Limitations of Use
OZOBAX DS is not indicated in the treatment of skeletal muscle spasm resulting from rheumatic disorders.

2 DOSAGE AND ADMINISTRATION

2.1 Important Dosage Information

Baclofen oral solution is available in multiple concentrations; ensure accuracy when prescribing, dispensing and administering baclofen oral solution to avoid dosing errors due to confusion between mg and mL, and with other baclofen oral solutions of different concentrations. When writing prescriptions, include both the total dose in mg and the total dose in volume.

2.2 Recommended Dosage

Initiate OZOBAX DS with a low dosage, preferably in divided doses, administered orally. The following gradually increasing dosage regimen is suggested, but should be adjusted based on clinical response and tolerability:

5 mg (2.5 mL) three times a day for three days

10 mg (5 mL) three times a day for three days

15 mg (7.5 mL) three times a day for three days

20 mg (10 mL) three times a day for three days

Additional increases may be necessary up to the maximum recommended dosage of 80 mg daily (20 mg four times a day).

2.3 Discontinuation of OZOBAX DS

When discontinuing OZOBAX DS, reduce the dosage slowly and avoid abrupt withdrawn from the drug to help minimize the risk of adverse reactions [see Warnings and Precautions (5.1)].

3 DOSAGE FORMS AND STRENGTHS

Oral Solution: 10 mg/5 mL baclofen as a clear, colorless solution

4 CONTRAINDICATIONS

OZOBAX DS is contraindicated in patients with hypersensitivity to baclofen.

5 WARNINGS AND PRECAUTIONS

5.1 Adverse Reactions from Abrupt Withdrawal of OZOBAX DS

Abrupt discontinuation of baclofen, regardless of the cause, has resulted in adverse reactions that include hallucinations, seizures, high fever, altered mental status, exaggerated rebound spasticity, and muscle rigidity, that in rare cases has advanced to rhabdomyolysis, multiple organ-system failure, and death. Therefore, reduce the dosage slowly when OZOBAX DS is discontinued, unless the clinical situation justifies a rapid withdrawal.

5.2 Neonatal Withdrawal Symptoms

Withdrawal symptoms in neonates whose mothers were treated with oral baclofen throughout pregnancy have been reported starting hours to days after delivery. The symptoms of withdrawal in these infants have included increased muscle tone, tremor, jitteriness, and seizure. If the potential benefit justifies the potential risk to the fetus and OZOBAX DS is continued during pregnancy, gradually reduce the dosage and discontinue OZOBAX DS before delivery. If slow withdrawal is not feasible, advise the parents or caregivers of the exposed neonate of the potential for neonatal withdrawal.

5.3 Drowsiness and Sedation

Drowsiness and sedation have been reported in up to 63% of patients taking baclofen, the active ingredient in OZOBAX DS [see Adverse Reactions (6.1)] . Patients should avoid operation of automobiles or other dangerous machinery and activities made hazardous by decreased alertness when starting OZOBAX DS or increasing the dose until they know how the drug affects them. Advise patients that the central nervous system depressant effects of OZOBAX DS may be additive to those of alcohol and other CNS depressants.

5.4 Poor Tolerability in Stroke Patients

OZOBAX DS should be used with caution in patients who have had a stroke. Baclofen has not significantly benefited patients with stroke. These patients have also shown poor tolerability to the drug.

5.5 Exacerbation of Psychotic Disorders, Schizophrenia, or Confusional States

OZOBAX DS should be used with caution in patients suffering from psychotic disorders, schizophrenia, or confusional states. If treated with OZOBAX DS, these patients should be kept under careful surveillance because exacerbations of these conditions have been observed with oral baclofen administration.

5.6 Exacerbation of Autonomic Dysreflexia

OZOBAX DS should be used with caution in patients with a history of autonomic dysreflexia. The presence of nociceptive stimuli or abrupt withdrawal of OZOBAX DS may cause an autonomic dysreflexic episode.

5.7 Exacerbation of Epilepsy

OZOBAX DS should be used with caution in patients with epilepsy. Deterioration in seizure control has been reported in patients taking baclofen.

5.8 Posture and Balance Effects

OZOBAX DS should be used with caution in patients where spasticity is utilized to sustain upright posture and balance in locomotion or whenever spasticity is utilized to obtain increased function.

5.9 Ovarian Cysts

A dose-related increase in incidence of ovarian cysts was observed in female rats treated chronically with oral baclofen. Ovarian cysts have been found by palpation in about 4% of the multiple sclerosis patients who were treated with oral baclofen for up to one year. In most cases, these cysts disappeared spontaneously while patients continued to receive the drug. Ovarian cysts are estimated to occur spontaneously in approximately 1% to 5% of the normal female population.

6 ADVERSE REACTIONS

The following clinically significant adverse reactions are described elsewhere in the labeling:

- Adverse Reactions from Abrupt Withdrawal of OZOBAX DS [see Warnings and Precautions (5.1)]
- Neonatal Withdrawal Symptoms [see Warnings and Precautions (5.2)]
- Drowsiness and Sedation [see Warnings and Precautions (5.3)]
- Poor Tolerability in Stroke Patients [see Warnings and Precautions (5.4)]
- Exacerbation of Psychotic Disorders, Schizophrenia, or Confusional States [see Warnings and Precautions (5.5)]
- Exacerbation of Autonomic Dysreflexia [see Warnings and Precautions (5.6)]
- Exacerbation of Epilepsy [see Warnings and Precautions (5.7)]
- Posture and Balance Effects [see Warnings and Precautions (5.8)]
- Ovarian Cysts [see Warnings and Precautions (5.9)]

6.1 Clinical Trials Experience

Because clinical trials are conducted under widely varying conditions, adverse reaction rates observed in the clinical trials of a drug cannot be directly compared to rates in the clinical trials of another drug and may not reflect the rates observed in practice.

The most common adverse reaction is transient drowsiness. In one controlled study of 175 patients, transient drowsiness was observed in 63% of those receiving baclofen compared to 36% of those in the placebo group. Other common adverse reactions (up to 15%) are dizziness and weakness. Adverse reactions with a frequency of ≥1% are listed in Table 1.

Table 1. Common (≥1%) Adverse Reactions in Patients Treated with Baclofen for Spasticity
ADVERSE REACTION | PERCENT
Drowsiness | 10-63%
Dizziness | 5-15%
Weakness | 5-15%
Nausea | 4-12%
Confusion | 1-11%
Hypotension | 0-9%
Headache | 4-8%
Insomnia | 2-7%
Constipation | 2-6%
Urinary Frequency | 2-6%
Fatigue | 2-4%

The following adverse reactions not included in Table 1, classified by body system, were also reported:

Neuropsychiatric: euphoria, excitement, depression, hallucinations, paresthesia, muscle pain, tinnitus, slurred speech, coordination disorder, tremor, rigidity, dystonia, ataxia, blurred vision, nystagmus, strabismus, miosis, mydriasis, diplopia, dysarthria, epileptic seizure

Cardiovascular: dyspnea, palpitation, chest pain, syncope

Gastrointestinal: dry mouth, anorexia, taste disorder, abdominal pain, vomiting, diarrhea, and positive test for occult blood in stool

Genitourinary: enuresis, urinary retention, dysuria, impotence, inability to ejaculate, nocturia, hematuria

Other: rash, pruritus, ankle edema, excessive perspiration, weight gain, nasal congestion

The following laboratory tests have been found to be abnormal in patients receiving baclofen: increased SGOT, elevated alkaline phosphatase, and elevation of blood sugar.

7 DRUG INTERACTIONS

7.1 CNS Depressants and Alcohol

OZOBAX DS can cause CNS depression, including drowsiness and sedation, which may be additive when used concomitantly with other CNS depressants or alcohol [see Warnings and Precautions (5.3)].

8 USE IN SPECIFIC POPULATIONS

8.1 Pregnancy

Risk Summary
There are no adequate data on the developmental risk associated with the use of OZOBAX DS in pregnant women. Oral administration of baclofen to pregnant rats resulted in an increased incidence of fetal structural abnormalities at a dose which was also associated with maternal toxicity. The background risk of major birth defects and miscarriage for the indicated population is unknown. In the U.S. general population, the estimated background risk of major birth defects and miscarriage in clinically recognized pregnancies is 2-4% and 15-20%, respectively.

Clinical Considerations
Fetal/Neonatal adverse reactions
Ozobax DS may increase the risk of late-onset neonatal withdrawal symptoms [see Warnings and Precautions (5.2)] .

Data

Animal Data
Baclofen given orally has been shown to increase the incidence of omphaloceles (ventral hernias) in fetuses of rats given approximately 13 times on a mg/kg basis, or 3 times on a mg/m ^2 basis, the maximum oral dose recommended for human use; this dose also caused reductions in food intake and weight gain in the dams. This abnormality was not seen in mice or rabbits.

8.2 Lactation

Risk Summary
At recommended oral doses, baclofen is present in human milk. There are no human data on the effects of baclofen on milk production. There are no adequate data on the effects of baclofen on the breastfed infant. Withdrawal symptoms can occur in breastfed infants when maternal administration of OZOBAX DS is stopped, or when breastfeeding is stopped [see Warnings and Precautions (5.2)] .

The developmental and health benefits of breastfeeding should be considered along with the mother’s clinical need for OZOBAX DS and any potential adverse effects on the breastfed infant from OZOBAX DS or from the underlying maternal condition.

8.4 Pediatric Use

Safety and effectiveness in pediatric patients below the age of 12 have not been established.

8.5 Geriatric Use

In general, dose selection for an elderly patient should be cautious, usually starting at the low end of the dosing range, reflecting the greater frequency of decreased hepatic, renal, or cardiac function, and of concomitant disease or other drug therapy.

8.6 Renal Impairment

Because baclofen is primarily excreted unchanged through the kidneys, OZOBAX DS should be given with caution to patients with renal impairment, and it may be necessary to reduce the dosage.

10 OVERDOSAGE

10.1 Symptoms of Baclofen Overdose

Patients may present in coma or with progressive drowsiness, lightheadedness, dizziness, somnolence, accommodation disorders, respiratory depression, seizures, or hypotonia progressing to loss of consciousness.

10.2 Treatment for Overdose

The treatment of baclofen overdose includes gastric decontamination, maintaining an adequate airway and respirations.

11 DESCRIPTION

OZOBAX DS (baclofen) oral solution is a gamma-aminobutyric acid (GABA-ergic) agonist available as 10 mg/5 mL solution for oral administration. Its chemical name is 4-amino-3-(4-chlorophenyl)-butanoic acid, and its structural formula is:

Molecular formula is C 1OH 12CINO 2.

Molecular Weight is 213.66.

Baclofen USP is a white to off-white, odorless or practically odorless crystalline powder. It is slightly soluble in water, very slightly soluble in methanol, and insoluble in chloroform.

The OZOBAX DS (baclofen) oral solution inactive ingredients are: glycerin, methylparaben, propylparaben, purified water, and sucralose. May also contain sodium hydroxide or hydrochloric acid for pH adjustment.

12 CLINICAL PHARMACOLOGY

12.1 Mechanism of Action

The precise mechanism of action of baclofen is not fully understood. Baclofen inhibits both monosynaptic and polysynaptic reflexes at the spinal level, possibly by decreasing excitatory neurotransmitter release from afferent terminals, although actions at supraspinal sites may also occur and contribute to its clinical effect. Baclofen is a structural analog of the inhibitory neurotransmitter gamma- aminobutyric acid (GABA), and may exert its effects by stimulation of the GABA B receptor subtype.

12.2 Pharmacodynamics

Baclofen has been shown to have general CNS depressant properties, as indicated by the production of sedation with tolerance, somnolence, ataxia, and respiratory and cardiovascular depression [see Warnings and Precautions (5.3), Adverse Reactions (6.1), and Overdosage (10.1)].

12.3 Pharmacokinetics

A pharmacokinetic study in heathy adult male subjects under fasting conditions at 20 mg dose level demonstrated similar bioavailability for baclofen oral solution (5 mg/5 mL) and oral tablets. The peak plasma concentrations were achieved in about 0.75 hours from oral solution and the apparent elimination half-life is about 5.7 hours. Baclofen is excreted primarily by the kidney in unchanged form, and there is relatively large intersubject variation in absorption and/or elimination.

13 NONCLINICAL TOXICOLOGY

13.1 Carcinogenesis, Mutagenesis, Impairment of Fertility

Carcinogenesis

No increase in tumors was seen in rats receiving baclofen orally for two years at approximately 30 to 60 times on a mg/kg basis, or 10 to 20 times on a mg/ m ^2 basis, the maximum oral dose recommended for human use.

Mutagenesis

Genetic toxicology assays have not been conducted for baclofen.

Impairment of Fertility

Studies to evaluate the effects of baclofen on fertility have not been conducted.

14 CLINICAL STUDIES

The efficacy of OZOBAX DS is based upon a bioavailability study in healthy adults comparing baclofen oral tablets to baclofen oral solution [see Clinical Pharmacology (12.3)].

16 HOW SUPPLIED/STORAGE AND HANDLING

16.1 How Supplied

OZOBAX DS (baclofen) Oral Solution contains 10 mg/5 mL baclofen. It is a clear, colorless solution and is supplied in bottles of 237 mL (NDC 69528-302-08) and 473 mL (NDC 69528-302-16).

16.2 Storage and Handling

Store at 20°C to 25°C (68°F to 77°F); excursions permitted to 15°C to 30°C (59°F to 86°F) [see USP Controlled Room Temperature]. Dispense in a tight, light-resistant container with a child-resistant closure.

17 PATIENT COUNSELING INFORMATION

Administration Instructions

Instruct patients or caregivers to use an oral dosing syringe to correctly measure the prescribed amount of medication. Inform patients that oral dosing syringes may be obtained from their pharmacy.

Risks Related to Sudden Withdrawal of OZOBAX DS

Advise patients and caregivers not to discontinue use of OZOBAX DS without consulting with their healthcare provider because sudden withdrawal of OZOBAX DS can result in serious complications that include hallucinations, seizures, high fever, confusion, muscle stiffness, multiple organ-system failure, and death [see Warnings and Precautions (5.1)]. Inform patients that early symptoms of OZOBAX DS withdrawal may include increased spasticity, itching, and tingling of extremities.

Neonatal Withdrawal Symptoms

Advise patients to notify their healthcare provider if they are pregnant, plan to become pregnant, or plan to breastfeed [see Warnings and Precautions (5.2) and Use in Specific Populations (8.2)].

Increased Risk of Drowsiness with Alcohol and Other CNS Depressants

Advise patients that OZOBAX DS may cause drowsiness, and that they should avoid the operation of automobiles or other dangerous machinery, or activities made hazardous by decreased alertness when starting OZOBAX DS or increasing the dose until they know how the drug affects them [see Warnings and Precautions (5.3)]. Inform patients and their caregivers that the drowsiness associated with OZOBAX DS use can be worsened by alcohol and other CNS depressants. Advise patients to read all medicine labels carefully, and to tell their healthcare provider about all prescription and nonprescription drugs they may use.

Manufactured by:

Delpharm Montreal, Inc.

3535 Route Trans Canada Highway

Pointe-Claire, QC, Canada H9R 1B4

Manufactured for:
Metacel Pharmaceuticals, LLC
Athens, GA 30601

OZOBAX ® is a registered U.S. trademark of Metacel Pharmaceuticals LLC

PACKAGE LABEL. PRINCIPAL DISPLAY PANEL

NDC 69528-302-08

OZOBAX ® DS

(baclofen)
Oral Solution

10 mg / 5 mL (2 mg/mL)

Baclofen oral solution is available in different concentrations
Clear liqud solution

RX only

8 fl. oz. (237 mL)

NDC 69528-302-16

OZOBAX ® DS

(baclofen)
Oral Solution

10 mg / 5 mL (2 mg/mL)

Baclofen oral solution is available in different concentrations
Clear liqud solution

RX only

16 fl. oz. (473 mL)